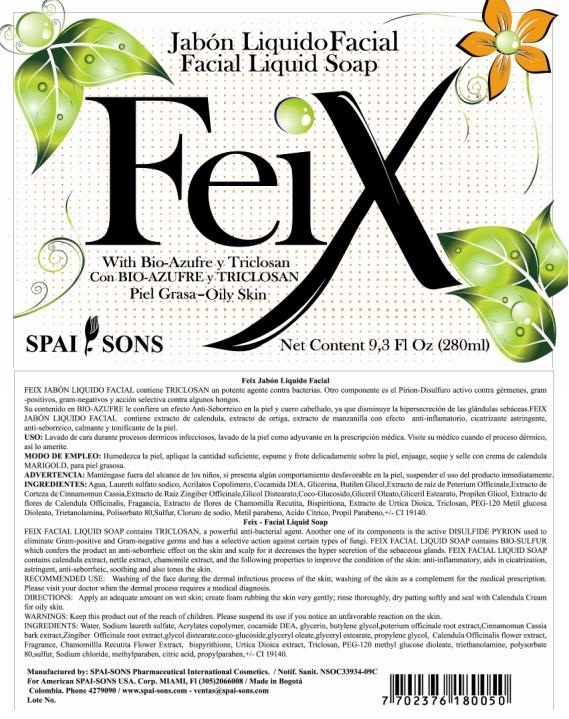 DRUG LABEL: FEIX
NDC: 66854-024 | Form: LIQUID
Manufacturer: SPAI-SONS PHARMACEUTICAL INTERNATIONAL COSMETICS
Category: otc | Type: HUMAN OTC DRUG LABEL
Date: 20120607

ACTIVE INGREDIENTS: SULFUR 0.2 mL/100 mL; DIPYRITHIONE 0.5 mL/100 mL
INACTIVE INGREDIENTS: WATER; SODIUM LAURETH SULFATE; COCO DIETHANOLAMIDE; GLYCERIN; BUTYLENE GLYCOL; SANGUISORBA OFFICINALIS ROOT; CHINESE CINNAMON; GINGER; GLYCOL DISTEARATE; COCO GLUCOSIDE; GLYCERYL OLEATE; GLYCERYL MONOSTEARATE; PROPYLENE GLYCOL; CALENDULA OFFICINALIS FLOWER  ; CHAMOMILE; URTICA DIOICA LEAF; TRICLOSAN; PEG-120 METHYL GLUCOSE DIOLEATE; TROLAMINE; POLYSORBATE 80; SODIUM CHLORIDE; METHYLPARABEN; CITRIC ACID MONOHYDRATE; PROPYLPARABEN; FD&C YELLOW NO. 5

FEIX JABON LIQUIDO FACIAL/ FACIAL LIQUID SOAP

ACTIVE INGREDIENT

Feix Facial Liquid soap contains TRICLOSAN, a powerful antibacterial agent. Another one of its components is the active DIPYRITHIONE and BIO-SULFUR used to eliminate Gram positive and Gram negative germs and has a selective action against certain types of fungi.

PURPOSE

Washing of the face during the dermal infectiuos process of the skin; washing of the skin as a complement for the medical prescription. Please visit your doctor when the dermal process requires a medical diagnosis

KEEP OUT OF REACH OF CHILDREN

Keep this product out of the reach of children

INDICATIONS AND USAGE

Facial soap used in persons with oily skin.

WARNINGS

Please suspend its use if you notice an unfavorable reaction on the skin

DOSAGE AND ADMINISTRATION

Apply an adequate amount on wet skin; create foam rubbing the skin very gently; rinse thoroughly, dry patting softly and seal with Calendula Cream for oily skin.

INACTIVE INGREDIENT

Contains calendula extract, nettle extract, chamomile extract, and following propierties to improve the condition of the skin: anti-inflamatory, aids in cicatrization, astringent, anti-seborrheic, soothing and also tones the skin.

IMAGE OF THE LABEL